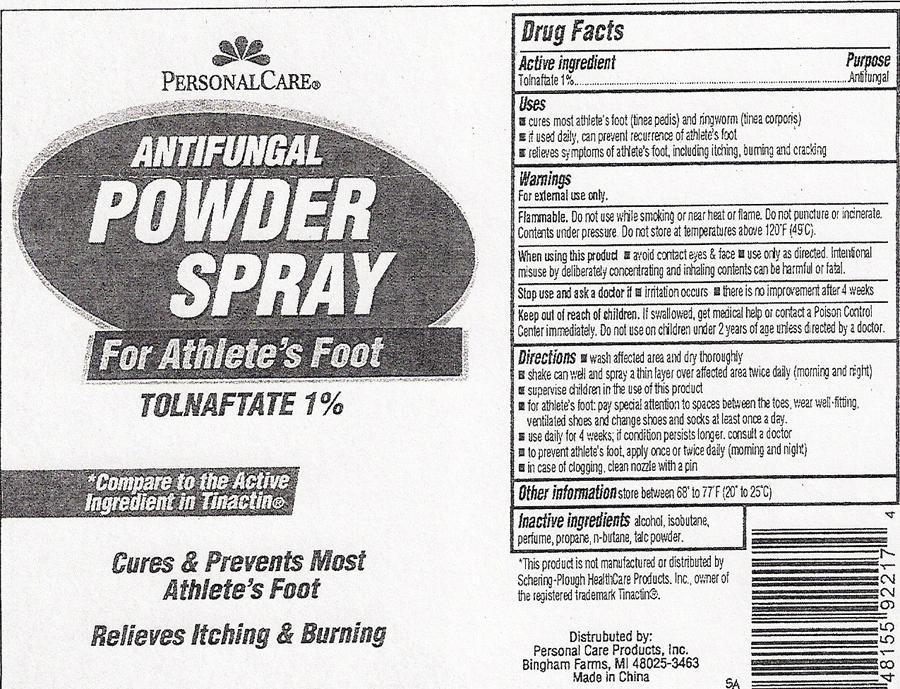 DRUG LABEL: Personal Care Antifungal
                
NDC: 29500-0035 | Form: SPRAY
Manufacturer: Personal Care Products, Inc.
Category: otc | Type: HUMAN OTC DRUG LABEL
Date: 20150901

ACTIVE INGREDIENTS: TOLNAFTATE 1 g/100 g
INACTIVE INGREDIENTS: ALCOHOL; ISOBUTANE; PROPANE; BUTANE; TALC

Drug Facts Active ingredient

Tolnaftate 1%

Purpose

Antifungal

Keep out of reach of children

If swallowed, get medical help or contact a Poison Control Center immediately. Do not use on children under 2 years of age unless directed by a doctor.

Uses

- cures most athlete's foot (tinea pedis) and ringworm (tinea corporis)
- if used daily, can prevent recurrence of athlete's foot
- relieves symptoms of athlete's foot, including itching, burning and cracking

Warnings

For external use only

Flammable. Do not use while smoking or near heat or flame. Do not puncture or incinerate. Contents under pressure Do not store in temperature above 120°F (49°C).

When using this product

- avoid contact eyes and face
- use only as directed. Intentional misuse by deliberately concentrating and inhaling contents can be harmfl or fatal.

Stop use and ask a doctor if

- irritation occurs
- there is no improvement after 4 weks

Directions

- wash affected area and dry thoroughly
- shake can well and spray a this layer over affected area twice daily (morning and night)
- supervise children in the use of this product
- for athlete's foot: pay special attention to the spaces between the toes, wear well-fitting, ventilated shoes and change shoes and socks at least once day.
- use daily for 4 weeks; if condition persists longer, consult a doctor
- to prevent athlete's foot, apply once or twice daily (morning and night)
- in case of clogging, clean nozzle with a pin

Other information

store between 68° to 77°F (20° to 25°C)

Inactive ingredients

alcohol, isobutane, perfume, propane, n-butane, talc powder.

ANTI FUNGAL POWDER SPRAY Label

PERSONAL CARE®

ANTIFUNGAL POWDER SPRAY
For Athlete's Foot

TOLNAFTATE 1%

*Compare to the Active Ingredients in Tinactin®

Cures and Prevents Most Athlete's Foot

Relieves Itching and Burning

*This product is not manufactured ir distributed by Schering-Plough HealthCare Products, Inc., owner of the registered trademark Tinactin®

Distributed by: Personal Care Products, Inc. Bingham Farms, MI 48025-3463

Made in China